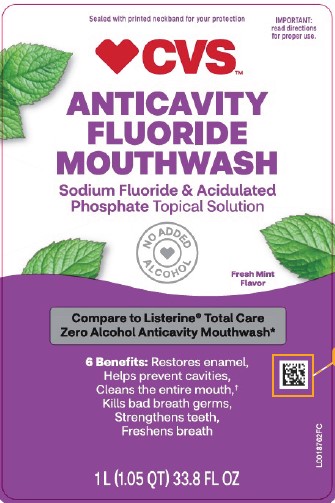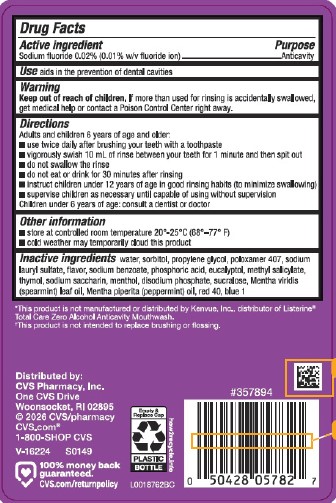 DRUG LABEL: Anticavity
NDC: 69842-548 | Form: RINSE
Manufacturer: CVS Pharmacy, Inc.
Category: otc | Type: HUMAN OTC DRUG LABEL
Date: 20260223

ACTIVE INGREDIENTS: SODIUM FLUORIDE 0.1 mg/1 mL
INACTIVE INGREDIENTS: WATER; SORBITOL; PROPYLENE GLYCOL; POLOXAMER 407; SODIUM LAURYL SULFATE; SODIUM BENZOATE; PHOSPHORIC ACID; EUCALYPTOL; METHYL SALICYLATE; THYMOL; SACCHARIN SODIUM; MENTHOL; SODIUM PHOSPHATE, DIBASIC, ANHYDROUS; SUCRALOSE; SPEARMINT OIL; PEPPERMINT OIL; FD&C RED NO. 40; FD&C BLUE NO. 1

CVS 971.001/971AB
Burn-Free Fluoride Anti-Cavity Mouthwash

Active ingredient

Sodium fluoride 0.02% (0.01% w/v fluoride ion)

Purpose

Anticavity

Use

aids in the prevention of dental cavities

Warning

For this product

Keep out of Reach of Children.

If more than used for rinsing is accidentally swallowed, get medical help or contact a Poison Control Center right away.

Directions

Adults and children 6 years of age and older:

- use twice daily after brushing your teeth with a toothpaste
- vigorously swish 10 mL of rinse between your teeth for 1 minute and then spit out
- do not swallow the rinse
- do not eat or drink for 30 minutes after rinsing
- instruct children under 12 years of age in good rinsing habits (to minimize swallowing)
- supervise children as necessary until capable of using without supervision

Children under 6 years of age: consult a dentist or doctor

Other information

- store at room temperature 20⁰ - 25⁰C (68⁰ - 77⁰F)
- cold weather may temporarily cloud this product

Inactive ingredients

water, sorbitol, propylene glycol, poloxamer 407, sodium lauryl sulfate, flavor, sodium benzoate, phosphoric acid, eucalyptol, methyl salicylate, thymol, sodium saccharin, menthol, disodium phosphate, sucralose, Mentha viridis (spearmint) leaf oil, Mentha piperita (peppermint) oil, red 40, blue 1

Disclaimers

*This product is not manufactured or distributed by Kenvue, Inc., distributor of Listerine®Total Care Zero Alcohol Anticavity Mouthwash.

†This product is not intended to replace brushing or flossing.

ADVERSE REACTION

Distributed by:

CVS Pharmacy, Inc.

One CVS Drive

Woonsocket, RI 02895

©2026 CVS/pharmacy

CVS.com®

1-800-SHOP CVS

100% money back guaranteed.

CVS.com/returnpolicy

Empty & Replace Cap

PLASTIC BOTTLE

how2recycle.info

Principal display panel

Sealed with printed neckband for your protection.

IMPORTANT: Read directions for proper use.

CVS™

Anticavity Fluoride Mouthwash

SODIUM FLUORIDE & ACIDULATED PHOSPHATE TOPCAL SOLUTION

NO ADDED ALCOHOL

Fresh Mint Flavor

Compare to Listerine®Total Care Zero Alcohol Anticavity Mouthwash*

6 Benefits:

- Restores enamel,
- Helps prevent cavities,
- Cleans the entire mouth,†
- Kills bad breath germs,
- Strengthens teeth,
- Freshens breath

1 L (1.05 QT) 33.8 FL OZ